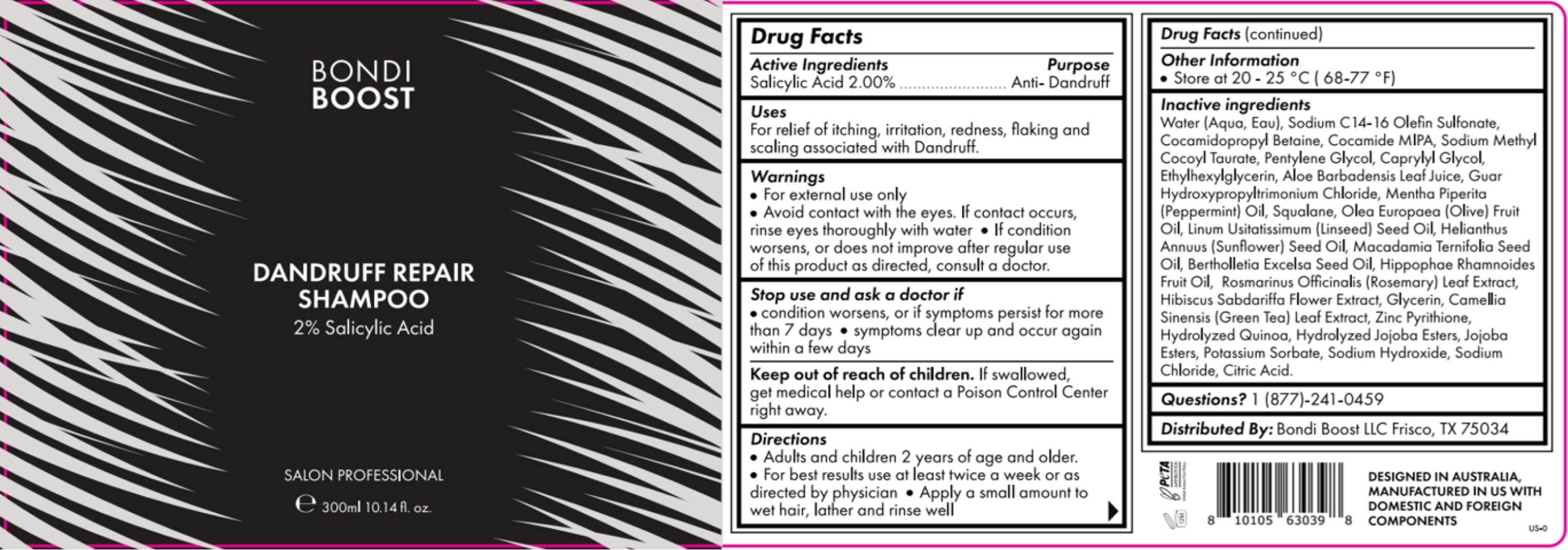 DRUG LABEL: S
NDC: 84169-001 | Form: SHAMPOO
Manufacturer: Bondi Boost U.s LLC
Category: otc | Type: HUMAN OTC DRUG LABEL
Date: 20241223

ACTIVE INGREDIENTS: SALICYLIC ACID 2 g/100 mL
INACTIVE INGREDIENTS: ROSEMARY; HIBISCUS SABDARIFFA FLOWER; GREEN TEA LEAF; SODIUM CHLORIDE; OLIVE OIL; PYRITHIONE ZINC; BRAZIL NUT OIL; SUNFLOWER OIL; GUAR HYDROXYPROPYLTRIMONIUM CHLORIDE; MENTHA PIPERITA; POTASSIUM SORBATE; HIPPOPHAE RHAMNOIDES FRUIT OIL; CITRIC ACID MONOHYDRATE; ALOE VERA LEAF; WATER; CAPRYLYL GLYCOL; ETHYLHEXYLGLYCERIN; SQUALENE; SODIUM C14-16 OLEFIN SULFONATE; COCO MONOISOPROPANOLAMIDE; HYDROLYZED JOJOBA ESTERS (ACID FORM); LINSEED OIL; GLYCERIN; COCAMIDOPROPYL BETAINE; SODIUM METHYL COCOYL TAURATE; PENTYLENE GLYCOL; MACADAMIA OIL; SODIUM HYDROXIDE; CHENOPODIUM QUINOA SEED

Bondi Boost Dandruff Repair Shampoo

Drug Facts

Active Ingredients | Purpose
Salicylic Acid 2.00% | Anti - Dandruff

Stop use and ask a doctor if

- Condition worsens, or if Symptoms persist for mre than 7 das
- symptoms clear up and occur again witin a few days

Keep Out of reach of children: If swallowed, get medica help or contact a Posion Control Center right away.

Questions?

Questions? 1 (877)-241-0459

Warnings

- For external use only
- Avoid contact with eyes. If contact occurs, rinse eyes thoroughly with water
- If condition worsens, or does not improve after regular use of this product as directed, consult a doctor.

STORAGE AND HANDLING

Store at 20 -25 °C (68- 77 ° F)

Inactive ingredients

Water (Aqua, Eau), Sodium C 14 -16 Olefin Sulfonate, Cocamidopropyl Betaine, Cocamide MIPA, Sodium Methyl Cocoyl Taurate, Pentylene Glycol, Caprylyl Glycol, Ethylhexylglycerin, Aloe Barbadensis Leaf Juice, Gaur Hydroxypropyltrimonium chloride, Mentha Piperita (Peppermint) Oil, Squalene, Olea Europaea (olive) fruit Oil, Linum Usitatissimum (Linseed) Seed Oil, Helianthus Annuus (Sunflower) Seed Oil, Macadamia Ternifolia Seed Oil, Bertholletia Excelsa Seed oil, Hippophae Rhamnoides Fruit Oil, Rosmarinus Officinalis (Rosemar) LEad Extract, Hibiscus Sabdariffa Flower Extract, Glycerin, Camellia Sinensis (Green Tea) Leaf Extract, Zinc Pyrithione, Hydrolyzed Quinoa, Hydrolyzed Jojoba Esters, Jojoba Esters, Potassium Sorbate, Sodium Hydroxide, Sodium Chloride, Citric acid.

INDICATIONS AND USAGE

For Relief of itching, irritation, rdness, flaking and scaling associated with Dandruff.

Directions:

Adults and children 2 years of age and older

For best results use at least twice a week or as directed by physician

Apply a small amount to wet hair, lather and rinse well